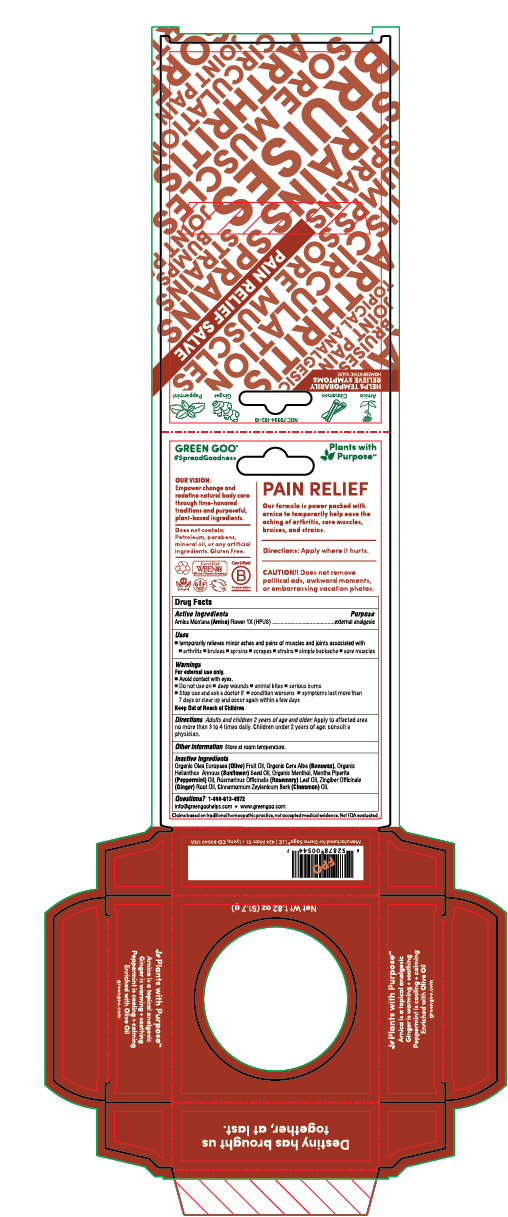 DRUG LABEL: Pain Relief
NDC: 70994-102 | Form: SALVE
Manufacturer: Spry Life LLC
Category: homeopathic | Type: HUMAN OTC DRUG LABEL
Date: 20251215

ACTIVE INGREDIENTS: ARNICA MONTANA FLOWER 1 [hp_X]/17 g
INACTIVE INGREDIENTS: OLIVE OIL; YELLOW WAX; SUNFLOWER OIL; MENTHOL; ROSEMARY OIL; CINNAMON OIL; GINGER OIL; MENTHA PIPERITA

Pain Relief

Purpose

External Analgesic

OTC Active Ingredients

Organic Arnica montana (Arnica) 1X (HPUS)

Indications & Usage

■ temporarily reief of minor aches and pains of muscles and joints associated with ■ arthritis ■ bruises ■ sprains ■ scrapes ■ strains ■ simple backache ■ sore muscles

Warnings

For external use only.

■ Avoid contact with eyes.
■ Do not use on ■ on deep wounds ■ animal bites ■ serious burns
■ Stop use and ask a doctor if ■ condition worsens ■ symptoms last more than 7 days or clear up and occur again within a few days

Keep Out of Reach of Children

Storage and Handling

Store at room temperature.

Dosage & Administration

Adults and children 2 years of age and older: Apply to affected area
not more than 3 to 4 times daily. Children under 2 years of age: consult a physician.

Inactive Ingredients

Organic Olea Europaea (Olive) Fruit Oil, Organic Cera Alba (Beeswax), Organic Helianthus Annuus (Sunflower) Seed Oil, Organic Menthol, Mentha Piperita (Peppermint) Oil, Rosmarinus Officinalis (Rosemary) Leaf Oil, Zingiber Officinale (Ginger) Root Oil, Cinnamomum Zeylanicum Bark (Cinnamon) Oil.